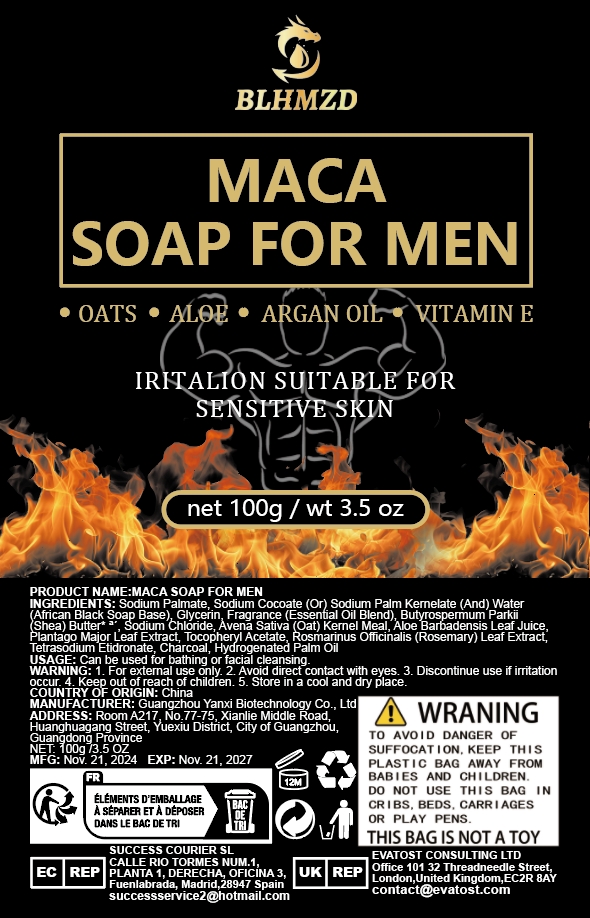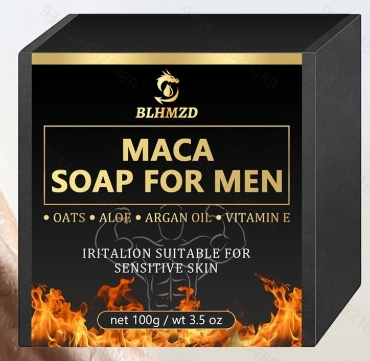 DRUG LABEL: Menssoap
NDC: 84025-309 | Form: SOAP
Manufacturer: Guangzhou Yanxi Biotechnology Co., Ltd
Category: otc | Type: HUMAN OTC DRUG LABEL
Date: 20250106

ACTIVE INGREDIENTS: RETINOL 5 mg/100 g; HYALURONIC ACID 3 mg/100 g
INACTIVE INGREDIENTS: WATER

DOSAGE AND ADMINISTRATION

Can be used for bathing or facial cleansing

WARNINGS

Keep out of children

INACTIVE INGREDIENT

Aqua

INDICATIONS AND USAGE

for daily face and body care

keep out of children

PURPOSE

Cleanse and moisturize your face and body.